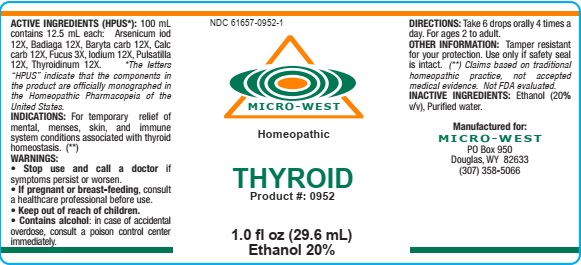 DRUG LABEL: Thyroid
NDC: 61657-0952 | Form: LIQUID
Manufacturer: White Manufacturing Inc. DBA Micro-West
Category: homeopathic | Type: HUMAN OTC DRUG LABEL
Date: 20210121

ACTIVE INGREDIENTS: IODINE 12 [hp_X]/30 mL; PULSATILLA VULGARIS 12 [hp_X]/30 mL; BARIUM CARBONATE 12 [hp_X]/30 mL; OYSTER SHELL CALCIUM CARBONATE, CRUDE 12 [hp_X]/30 mL; THYROID, UNSPECIFIED 12 [hp_X]/30 mL; ARSENIC TRIIODIDE 12 [hp_X]/30 mL; FUCUS VESICULOSUS 3 [hp_X]/30 mL; SPONGILLA LACUSTRIS 12 [hp_X]/30 mL
INACTIVE INGREDIENTS: ALCOHOL

DRUG FACTS

ACTIVE INGREDIENTS

Arsenicum iod 12X

Badiaga 12X

Baryta carb 12X

Calc carb 12X

Fucus 3X

Iodium 12X

Pulsatilla 12X

Thyroidinum 12X

INACTIVE INGREDIENTS

Alcohol (20% v/v, Purified water

PURPOSE

FOR MENTAL, MENSES,SKIN AND IMMUNE SYSTEM CONDITIONS ASSOCIATED WITH THYROID HOMEOSTASIS

KEEP OUT OF REACH OF CHILDREN

INDICATIONS

INDICATIONS:For the temporary relief of mental, menses, skin, and immune system conditions associated with thyroid homeostasis

WARNING

WARNING: STOP USE AND CALL A DOCTOR if symptoms persist or worsen. IF PREGNANT OR BREAST-FEEDING, consult a healthcare professional before use. CONTAINS ALCOHOL, in case of accidental overdose, consult a poison control center immediately.

OTHER SAFETY INFORMATION

OTHER INFORMATION: Tamper resistant for your protection. Use only if safety seal is intact.

DIRECTIONS

DIRECTIONS: Take 6 drops orally, 4 times a day. For ages 12 to adult

MANUFACTURE

MANUFACTURED FOR

MICRO-WEST

P.O. Box 950

DOUGLAS, WY 82633

1-307-358-5066

LABEL

NDC 61657-0952-1

MICRO-WEST

Homeopathic

THYROID

1.0 fl oz (29.6 mL)

Ethanol 20%